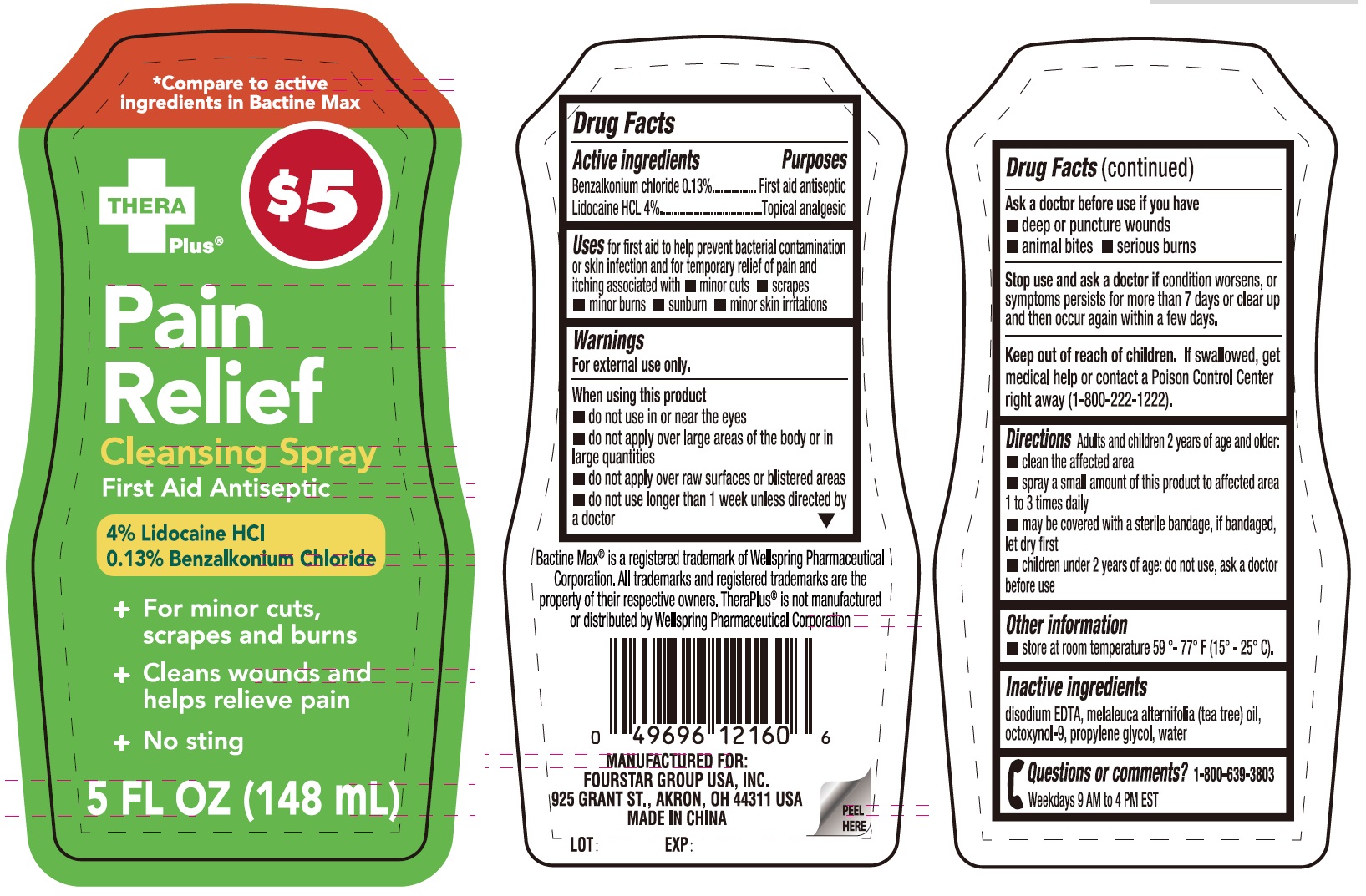 DRUG LABEL: Thera Plus Pain Relief Cleansing
NDC: 80684-150 | Form: LIQUID
Manufacturer: Fourstar Group USA, Inc.
Category: otc | Type: HUMAN OTC DRUG LABEL
Date: 20250304

ACTIVE INGREDIENTS: BENZALKONIUM CHLORIDE 1.3 mg/1 mL; LIDOCAINE HYDROCHLORIDE 40 mg/1 mL
INACTIVE INGREDIENTS: EDETATE DISODIUM; MELALEUCA ALTERNIFOLIA LEAF; OCTOXYNOL-9; PROPYLENE GLYCOL; WATER

Thera Plus Pain Relief Cleansing Spray

Active ingredients

Benzalkonium chloride 0.13%

Lidocaine HCL 4%

Purpose

First aid antiseptic

Topical analgesic

Uses

for first aid to help prevent bacterial contamination or skin infection and for temporary relief of pain and itching associated with

- mionr cuts
- scrapes
- minor burns
- sunburn
- minor skin irritations

Warnings

For external use only.

When using this product

- do not use in or near the eyes
- do not apply over large areas of the body or in large quantities
- do not apply over raw surfaces or blistered areas
- do not use longer than 1 week unless directed by a doctor

Ask a doctor before use if you have

- deep or puncture wounds
- animal bites
- serious burns

Stop use and ask a doctor if

condition worsens, or symptoms persists for more than 7 days or clear up and then occur again within a few days.

Keep out of reach of children.

If swallowed, get medical help or contact a Poison Control Center right away (1-800-222-1222).

Directions

Adults and children 2 years of age and older:

- clean the affected area
- spray a small amount of this product to affected area 1 to 3 times daily
- may be covered with a sterile bandage, if bandaged, let dry first
- children under 2 years of age: do not use, ask a doctor before use

Other information

- store at room temperature 59º - 77º F (15º- 25º C).

Inactive ingredients

disodium EDTA, melaleuca alternifolia (tea tree) oil, octoxynol-9, propylene glycol, water

Questions or comments?

1-800-639-3803

Weekdays 9 AM to 4 PM EST